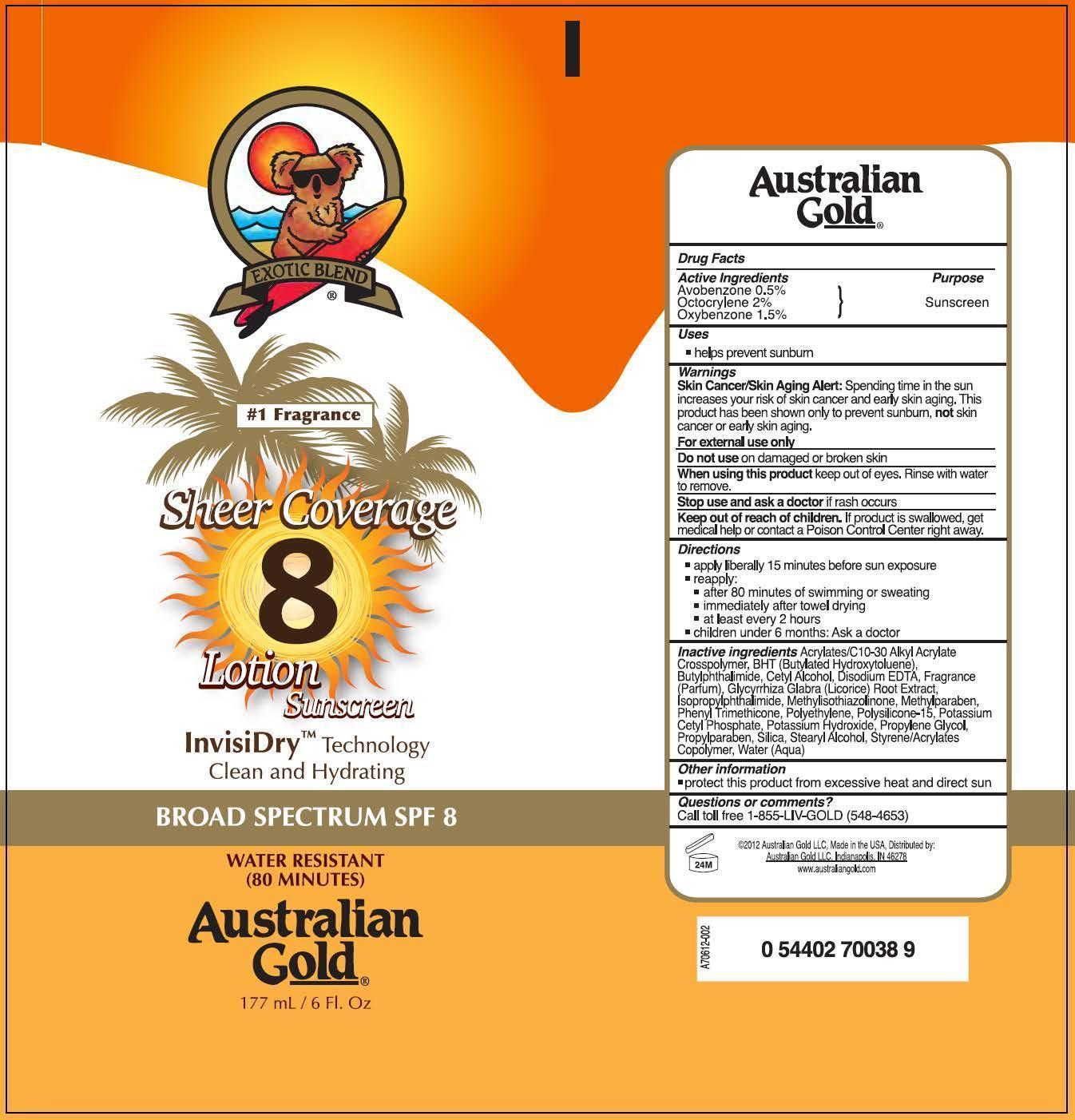 DRUG LABEL: Australian Gold
NDC: 58443-0029 | Form: LOTION
Manufacturer: Prime Enterprises, Inc.
Category: otc | Type: HUMAN OTC DRUG LABEL
Date: 20200117

ACTIVE INGREDIENTS: AVOBENZONE 4.9 mg/1 mL; OCTOCRYLENE 19.4 mg/1 mL; OXYBENZONE 14.6 mg/1 mL
INACTIVE INGREDIENTS: CARBOMER COPOLYMER TYPE A; BUTYLATED HYDROXYTOLUENE; 3-BUTYLPHTHALIDE; ISOPROPYLPHTHALIMIDE; CETYL ALCOHOL; EDETATE DISODIUM; METHYLISOTHIAZOLINONE; METHYLPARABEN; PHENYL TRIMETHICONE; HIGH DENSITY POLYETHYLENE; POLYSILICONE-15; POTASSIUM CETYL PHOSPHATE; POTASSIUM HYDROXIDE; PROPYLENE GLYCOL; WATER; GLYCYRRHIZA GLABRA LEAF; PROPYLPARABEN; SILICON DIOXIDE; STEARYL ALCOHOL; STYRENE

Active ingredients

Avobenzone 0.5 %, Octocrylene 2 %, and Oxybenzone 1.5 %

Purpose

Sunscreen

Uses

- helps prevent sunburn

Warnings

Skin Cancer/Skin Aging Alert: Spending time in the sun increases your risk of skin cancer and early skin aging. This product has been shown only to prevent sunburn, not skin cancer or early skin aging.

OTHER SAFETY INFORMATION

For external use only

Do not use on damaged or broken skin.

When using this product keep out of eyes. Rinse with water to remove.

Stop use and ask a doctor if rash occurs.

Keep out of reach of children. If product is swallowed, get medical help or contact a Poison Control Center right away.

Directions

- apply liberally 15 minutes before sun exposure
- reapply:
  - after 80 minutes of swimming or sweating
  - immediately after towel drying
  - at least every 2 hours
- Children under 6 months: Ask a doctor

Inactive Ingredients

Acrylates/C10-30 Alkyl Acrylate Crosspolymer, BHT (Butylated Hydroxytoluene), Butylphthalimide, Cetyl Alcohol, Disodium EDTA, Fragrance (Parfum), Glycyrrhiza Glabra (Licorice) Root Extract, Isopropylphthalimide, Methylisothiazolinone, Methylparaben, Phenyl Trimethicone, Polyethylene, Polysilicone-15, Potassium Cetyl Phosphate, Potassium Hydroxide, Propylene Glycol, Propylparaben, Silica, Stearyl Alcohol, Styrene/Acrylates Copolymer, Water (Aqua)

Other information

- protect this product from excesive heat and direct sun

Questions or Comments?

Call toll free 1-855-LIV-GOLD (548-4653)

PRINCIPAL DISPLAY PANEL - 177 mL Tube Label

EXOTIC BLEND

#1 Fragrance

Sheer Coverage

8

Lotion Sunscreen

InvisiDry Technology

Clean and Hydrating

Broad Spectrum SPF 8

WATER RESISTANT

(80 MINUTES)

Australian

Gold

177 mL / 6 Fl. Oz